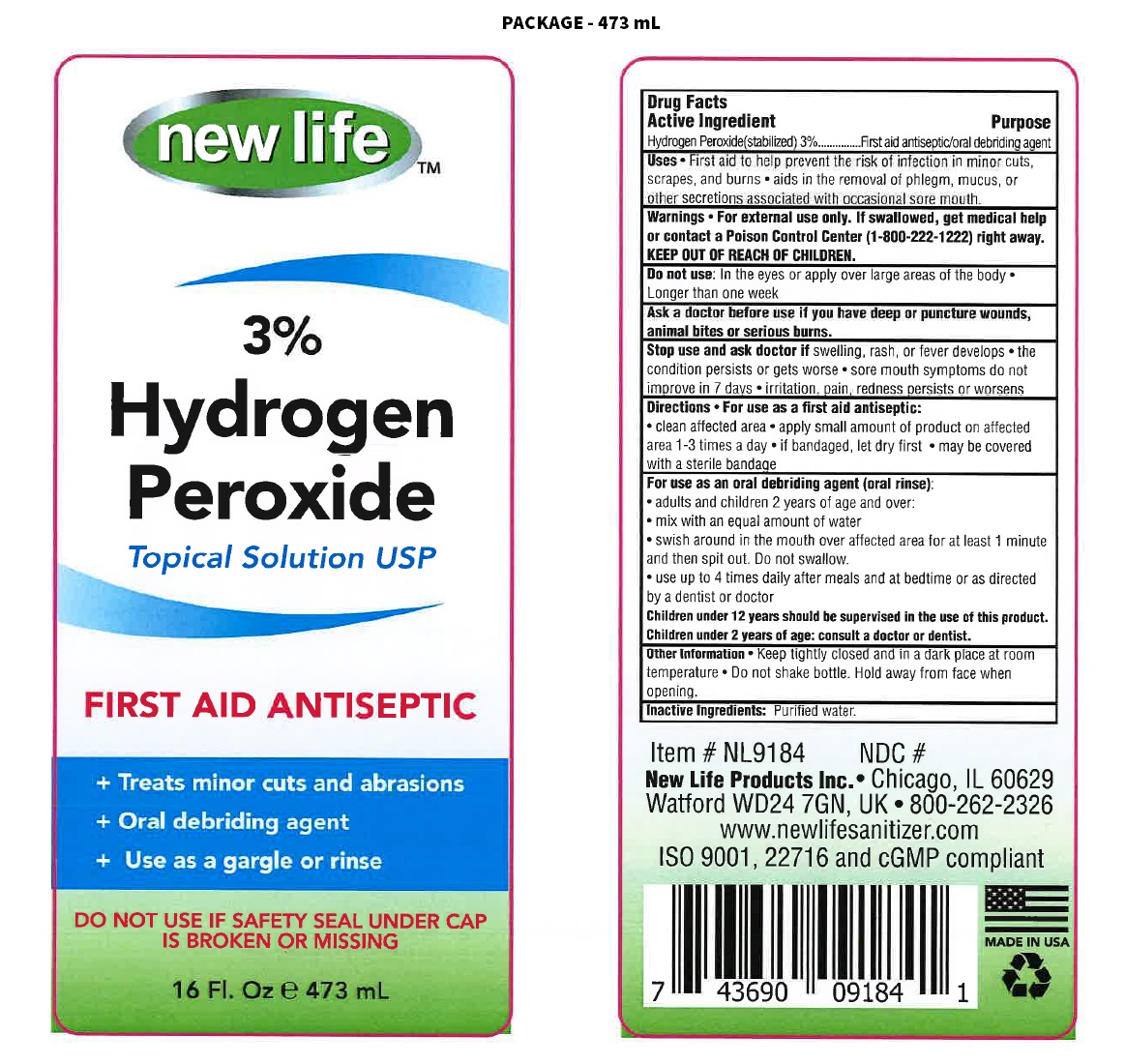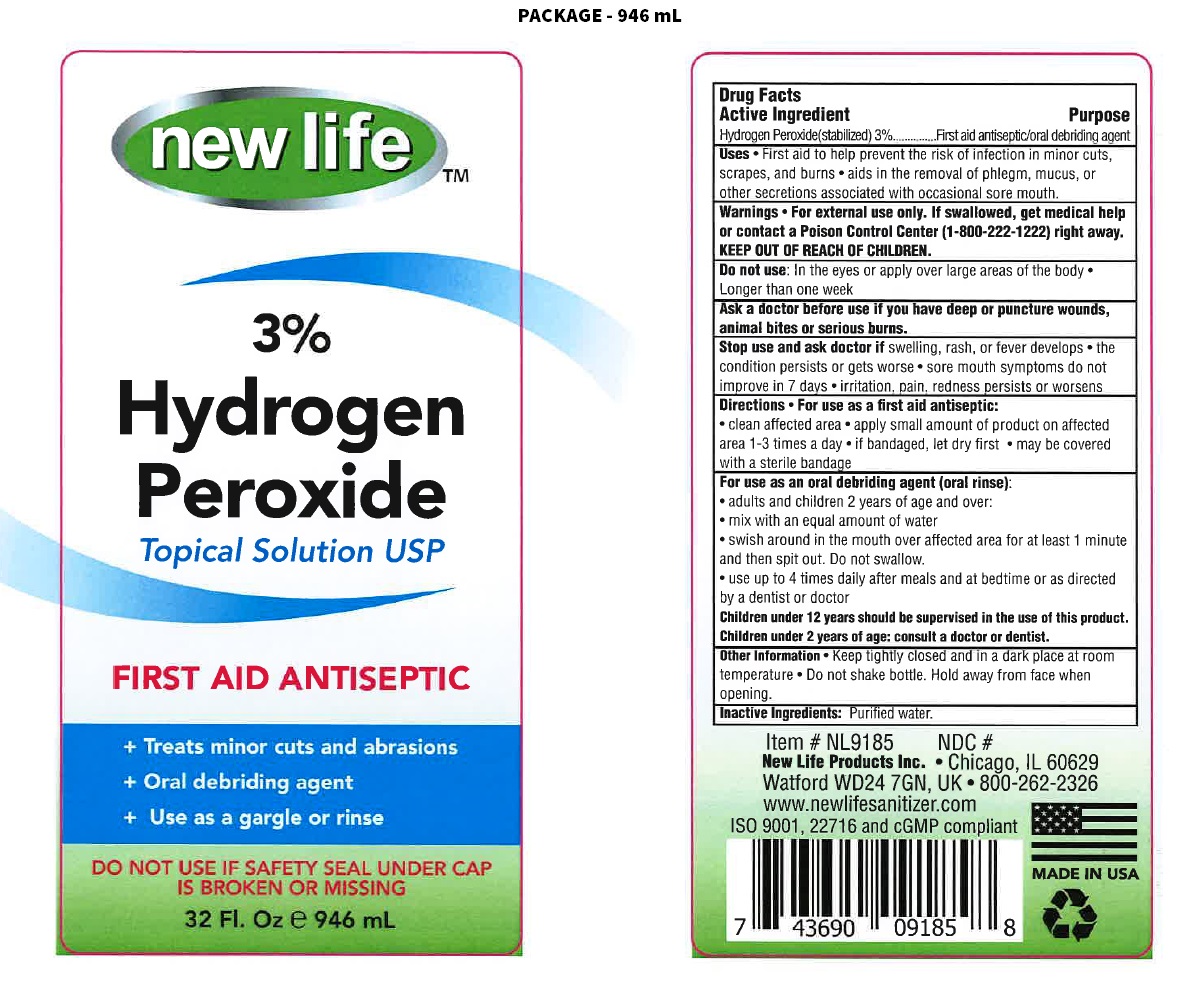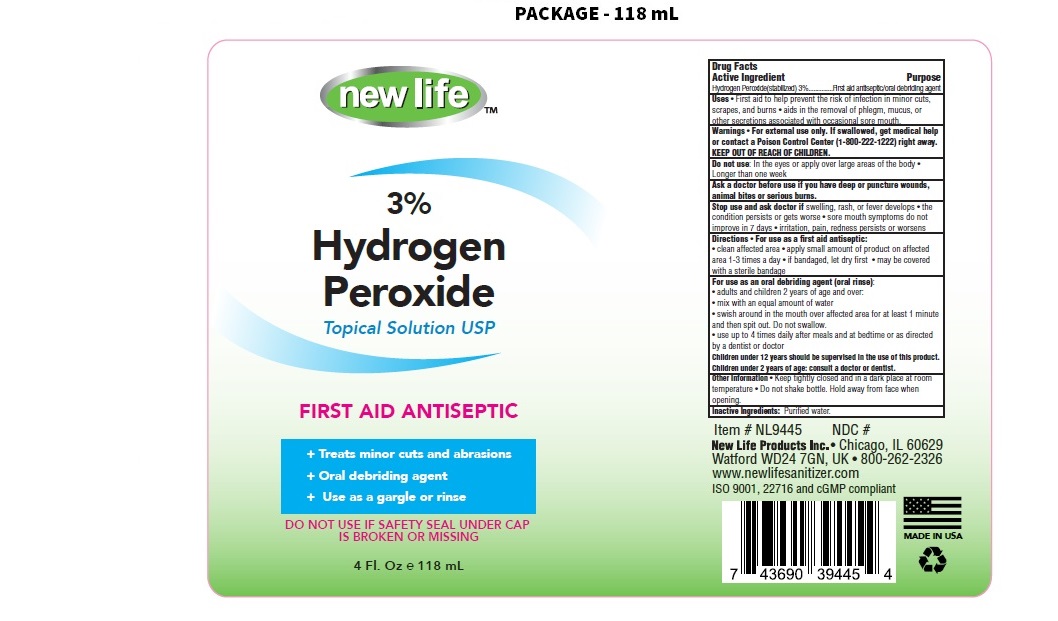 DRUG LABEL: New Life 3% Hydrogen Peroxide FIRST AID ANTISEPTIC
NDC: 49681-016 | Form: SOLUTION
Manufacturer: New Life Products, Inc.
Category: otc | Type: HUMAN OTC DRUG LABEL
Date: 20230202

ACTIVE INGREDIENTS: HYDROGEN PEROXIDE 3 mL/100 mL
INACTIVE INGREDIENTS: WATER

new life™ 3% Hydrogen Peroxide

Active Ingredient

Hydrogen Peroxide(stabilized) 3%

Purpose

First aid antiseptic/oral debriding agent

Uses

• First aid to help prevent the risk of infection in minor cuts, scrapes and burns • aids in the removal of phlegm, mucus, or other secretions associated with occasional sore mouth.

Warnings

• For external use only. If swallowed, get medical help or contact a Poison Control Center (1-800-222-1222) right away.

Do not use: In the eyes or apply over large areas of the body • Longer than one week

Ask a doctor before use if you have deep or puncture wounds, animal bites or serious burns.

Stop use and ask a doctor if swelling, rash, or fever develops • the condition persists or gets worse • sore mouth symptoms do not improve in 7 days • irritation, pain, redness persists or worsens

KEEP OUT OF REACH OF CHILDREN.

Directions

• For use as a first aid antiseptic:

• clean affected area • apply small amount of product on affected area 1 to 3 times a day • if bandaged, let dry first • may be covered with a sterile bandage

For use as an oral debriding agent (oral rinse):

• adults and children 2 years of age and over:

• mix with an equal amount of water

• swish around in the mouth over the affected area for at least 1 minute and then spit out. Do not swallow.

• use up to 4 times daily after meals and at bedtime or as directed by a dentist or doctor

Children under 12 years should be supervised in the use of this product.

Children under 2 years of age: consult a doctor or dentist.

Other Information

• Keep tightly closed and in a dark place at room temperature • Do not shake bottle. Hold away from face when opening.

Inactive Ingredients:

Purified water.

Topical Solution USP

FIRST AID ANTISEPTIC

+ Treats minor cuts and abrasions

+ Oral debriding agent

+ Use as a gargle or rinse

DO NOT USE IF SAFETY SEAL UNDER CAP IS BROKEN OR MISSING

New Life Products Inc. • Chicago, IL 60629
Watford WD24 7GN, UK • 800-262-2326
www.newlifesanitizer.com

ISO 9001, 22716 and cGMP compliant

MADE IN USA